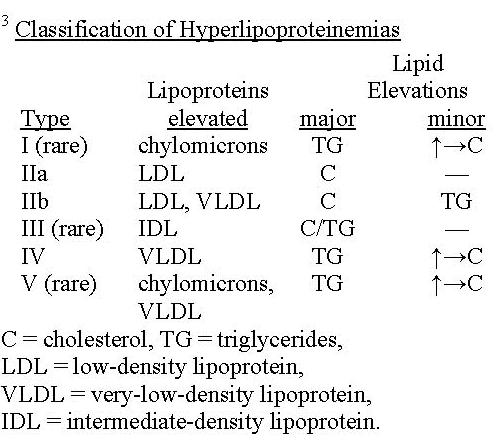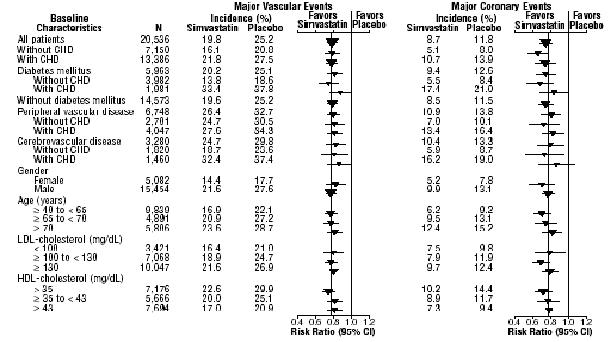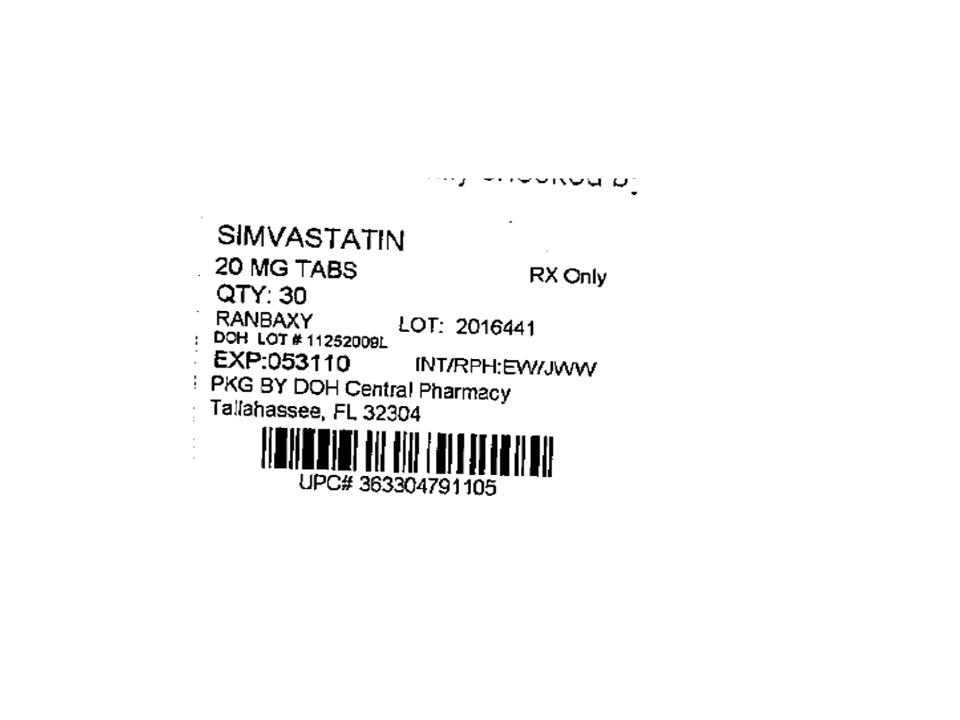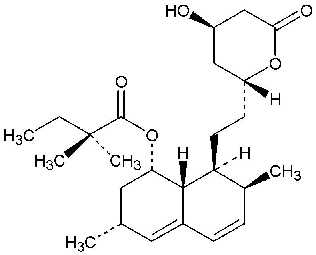 DRUG LABEL: Simvastatin
NDC: 53808-0793 | Form: TABLET, FILM COATED
Manufacturer: State of Florida DOH Central Pharmacy
Category: prescription | Type: HUMAN PRESCRIPTION DRUG LABEL
Date: 20100413

ACTIVE INGREDIENTS: SIMVASTATIN 20 mg/1 1
INACTIVE INGREDIENTS: ASCORBIC ACID; BUTYLATED HYDROXYANISOLE; CITRIC ACID MONOHYDRATE; CROSCARMELLOSE SODIUM; HYDROXYPROPYL CELLULOSE; HYPROMELLOSE; ISOPROPYL ALCOHOL; LACTOSE MONOHYDRATE; MAGNESIUM STEARATE; CELLULOSE, MICROCRYSTALLINE; STARCH, CORN; TALC; TITANIUM DIOXIDE

SIMVASTATIN
TABLETS

DESCRIPTION

Simvastatin is a lipid-lowering agent that is derived synthetically from a fermentation product of Aspergillus terreus. After oral ingestion, simvastatin, which is an inactive lactone, is hydrolyzed to the corresponding β-hydroxyacid form. This is an inhibitor of 3-hydroxy-3-methylglutaryl-coenzyme A (HMG-CoA) reductase. This enzyme catalyzes the conversion of HMG-CoA to mevalonate, which is an early and rate-limiting step in the biosynthesis of cholesterol.

Simvastatin is butanoic acid, 2,2-dimethyl-,1,2,3,7,8,8a-hexahydro-3,7-dimethyl-8-[2-(tetrahy-dro-4-hydroxy-6-oxo-2H-pyran-2-yl)-ethyl]-1-naphthalenyl ester, [1S-[1α,3α,7β,8β(2S*,4S*),-8aβ]]. The molecular formula of simvastatin is C25H38O5 and its molecular weight is 418.57. Its structural formula is:

Simvastatin is a white to off-white, nonhygroscopic, crystalline powder that is practically insoluble in water, and freely soluble in chloroform, methanol and ethanol.

Simvastatin tablets for oral administration contain either 5 mg, 10 mg, 20 mg, 40 mg and 80 mg of simvastatin and the following inactive ingredients: ascorbic acid, butylated hydroxyanisole, citric acid, croscarmellose sodium, hydroxypropyl cellulose, hypromellose, iron oxides, isopropyl alcohol, lactose monohydrate, magnesium stearate, microcrystalline cellulose, pregelatinized starch, talc and titanium dioxide.

CLINICAL PHARMACOLOGY

Epidemiological studies have demonstrated that elevated levels of total cholesterol (total-C), low-density lipoprotein cholesterol (LDL-C), as well as decreased levels of high-density lipoprotein cholesterol (HDL-C) are associated with the development of atherosclerosis and increased cardiovascular risk. Lowering LDL-C decreases this risk. However, the independent effect of raising HDL-C or lowering TG on the risk of coronary and cardiovascular morbidity and mortality has not been determined.

Pharmacokinetics

Simvastatin is a lactone that is readily hydrolyzed in vivo to the corresponding β-hydroxyacid, a potent inhibitor of HMG-CoA reductase. Inhibition of HMG-CoA reductase is the basis for an assay in pharmacokinetic studies of the β-hydroxyacid metabolites (active inhibitors) and, following base hydrolysis, active plus latent inhibitors (total inhibitors) in plasma following administration of simvastatin.

Following an oral dose of ^14C-labeled simvastatin in man, 13% of the dose was excreted in urine and 60% in feces. Plasma concentrations of total radioactivity (simvastatin plus ^14C-metabolites) peaked at 4 hours and declined rapidly to about 10% of peak by 12 hours postdose. Since simvastatin undergoes extensive first-pass extraction in the liver, the availability of the drug to the general circulation is low (< 5%).

Both simvastatin and its β-hydroxyacid metabolite are highly bound (approximately 95%) to human plasma proteins. Rat studies indicate that when radiolabeled simvastatin was administered, simvastatin-derived radioactivity crossed the blood-brain barrier.

The major active metabolites of simvastatin present in human plasma are the β-hydroxyacid of simvastatin and its 6′-hydroxy, 6′-hydroxymethyl, and 6′-exomethylene derivatives. Peak plasma concentrations of both active and total inhibitors were attained within 1.3 to 2.4 hours postdose. While the recommended therapeutic dose range is 5 to 80 mg/day, there was no substantial deviation from linearity of AUC of inhibitors in the general circulation with an increase in dose to as high as 120 mg. Relative to the fasting state, the plasma profile of inhibitors was not affected when simvastatin was administered immediately before an American Heart Association recommended low-fat meal.

In a study including 16 elderly patients between 70 and 78 years of age who received simvastatin 40 mg/day, the mean plasma level of HMG-CoA reductase inhibitory activity was increased approximately 45% compared with 18 patients between 18 to 30 years of age. Clinical study experience in the elderly (n = 1522), suggests that there were no overall differences in safety between elderly and younger patients (see PRECAUTIONS, Geriatric Use).

Kinetic studies with another reductase inhibitor, having a similar principal route of elimination, have suggested that for a given dose level higher systemic exposure may be achieved in patients with severe renal insufficiency (as measured by creatinine clearance).

In a study of 12 healthy volunteers, simvastatin at the 80 mg dose had no effect on the metabolism of the probe cytochrome P450 isoform 3A4 (CYP3A4) substrates midazolam and erythromycin. This indicates that simvastatin is not an inhibitor of CYP3A4, and, therefore, is not expected to affect the plasma levels of other drugs metabolized by CYP3A4.

Although the mechanism is not fully understood, cyclosporine has been shown to increase the AUC of HMG-CoA reductase inhibitors. The increase in AUC for simvastatin acid is presumably due, in part, to inhibition of CYP3A4.

The risk of myopathy is increased by high levels of HMG-CoA reductase inhibitory activity in plasma. Potent inhibitors of CYP3A4 can raise the plasma levels of HMG-CoA reductase inhibitory activity and increase the risk of myopathy (see WARNINGS, Myopathy/Rhabdomyolysis and PRECAUTIONS, Drug Interactions).

Gemfibrozil: Coadministration of gemfibrozil (600 mg twice daily for 3 days) with simvastatin (40 mg daily) resulted in clinically significant increases in simvastatin acid AUC (185%) and Cmax (112%), possibly due to inhibition of simvastatin acid glucuronidation by gemfibrozil (see WARNINGS, Myopathy/Rhabdomyolysis, PRECAUTIONS, Drug Interactions, DOSAGE AND ADMINISTRATION).

Fenofibrate: Coadministration of fenofibrate (160 mg daily) with simvastatin (80 mg daily) for 7 days had no effect on plasma AUC (and Cmax) of either total HMG-CoA reductase inhibitory activity or fenofibric acid; there was a modest reduction (approximately 35%) of simvastatin acid which was not considered clinically significant (see WARNINGS, Myopathy/Rhabdomyolysis, PRECAUTIONS, Drug Interactions).

Simvastatin is a substrate for CYP3A4 (see PRECAUTIONS, Drug Interactions). Grapefruit juice contains one or more components that inhibit CYP3A4 and can increase the plasma concentrations of drugs metabolized by CYP3A4. In one study [Lilja JJ, Kivisto KT, Neuvonen PJ. Clin Pharmacol Ther 1998;64(5):477-83] , 10 subjects consumed 200 mL of double-strength grapefruit juice (one can of frozen concentrate diluted with one rather than 3 cans of water) three times daily for 2 days and an additional 200 mL double-strength grapefruit juice together with, and 30 and 90 minutes following, a single dose of 60 mg simvastatin on the third day. This regimen of grapefruit juice resulted in mean increases in the concentration (as measured by the area under the concentration-time curve) of active and total HMG-CoA reductase inhibitory activity [measured using a radioenzyme inhibition assay both before (for active inhibitors) and after (for total inhibitors) base hydrolysis] of 2.4-fold and 3.6-fold, respectively, and of simvastatin and its β-hydroxyacid metabolite [measured using a chemical assay — liquid chromatography/tandem mass spectrometry] of 16-fold and 7-fold, respectively. In a second study, 16 subjects consumed one 8 oz glass of single-strength grapefruit juice (one can of frozen concentrate diluted with 3 cans of water) with breakfast for 3 consecutive days and a single dose of 20 mg simvastatin in the evening of the third day. This regimen of grapefruit juice resulted in a mean increase in the plasma concentration (as measured by the area under the concentration-time curve) of active and total HMG-CoA reductase inhibitory activity [using a validated enzyme inhibition assay different from that used in the first study, both before (for active inhibitors) and after (for total inhibitors) base hydrolysis] of 1.13-fold and 1.18-fold, respectively, and of simvastatin and its β-hydroxyacid metabolite [measured using a chemical assay — liquid chromatography/tandem mass spectrometry] of 1.88-fold and 1.31-fold, respectively. The effect of amounts of grapefruit juice between those used in these two studies on simvastatin pharmacokinetics has not been studied.

Reductions in Risk of CHD Mortality and Cardiovascular Events

In 4S, the effect of therapy with simvastatin on total mortality was assessed in 4,444 patients with CHD and baseline total cholesterol 212 to 309 mg/dL (5.5 to 8 mmol/L). In this multicenter, randomized, double-blind, placebo-controlled study, patients were treated with standard care, including diet, and either simvastatin 20 to 40 mg/day (n = 2,221) or placebo (n = 2,223) for a median duration of 5.4 years. After six weeks of treatment with simvastatin the median (25th and 75th percentile) changes in LDL-C, TG, and HDL-C were -39% (-46, -31%), -19% (-31, 0%), and 6% (-3, 17%). Over the course of the study, treatment with simvastatin led to mean reductions in total-C, LDL-C and TG of 25%, 35%, and 10%, respectively, and a mean increase in HDL-C of 8%. Simvastatin significantly reduced the risk of mortality by 30% (p = 0.0003, 182 deaths in the simvastatin group vs 256 deaths in the placebo group). The risk of CHD mortality was significantly reduced by 42% (p = 0.00001, 111 vs 189 deaths). There was no statistically significant difference between groups in non-cardiovascular mortality. Simvastatin also significantly decreased the risk of having major coronary events (CHD mortality plus hospital-verified and silent non-fatal myocardial infarction [MI]) by 34% (p <0.00001, 431 vs 622 patients with one or more events). The risk of having a hospital-verified non-fatal MI was reduced by 37%.simvastatin significantly reduced the risk for undergoing myocardial revascularization procedures (coronary artery bypass grafting or percutaneous transluminal coronary angioplasty) by 37% (p <0.00001, 252 vs 383 patients). Furthermore, simvastatin significantly reduced the risk of fatal plus non-fatal cerebrovascular events (combined stroke and transient ischemic attacks) by 28% (p = 0.033, 75 vs 102 patients). simvastatin reduced the risk of major coronary events to a similar extent across the range of baseline total and LDL cholesterol levels. Because there were only 53 female deaths, the effect of simvastatin on mortality in women could not be adequately assessed. However, simvastatin significantly lessened the risk of having major coronary events by 34% (60 vs 91 women with one or more event). The randomization was stratified by angina alone (21% of each treatment group) or a previous MI. Because there were only 57 deaths among the patients with angina alone at baseline, the effect of simvastatin on mortality in this subgroup could not be adequately assessed. However, trends in reduced coronary mortality, major coronary events and revascularization procedures were consistent between this group and the total study cohort. Additionally, in this study, 1,021 of the patients were 65 and older. Cholesterol reduction with simvastatin resulted in similar decreases in relative risk for total mortality, CHD mortality, and major coronary events in these elderly patients, compared with younger patients.

The Heart Protection Study (HPS) was a large, multi-center, placebo-controlled, double-blind study with a mean duration of 5 years conducted in 20,536 patients (10,269 on simvastatin 40 mg and 10,267 on placebo). Patients were allocated to treatment using a covariate adaptive method [D.R. Taves, Minimization: a new method of assigning patients to treatment and control groups. Clin. Pharmacol. Ther. 15 (1974), pp. 443-453] which took into account the distribution of 10 important baseline characteristics of patients already enrolled and minimized the imbalance of those characteristics across the groups. Patients had a mean age of 64 years (range 40 to 80 years), were 97% Caucasian and were at high risk of developing a major coronary event because of existing coronary heart disease (65%), diabetes (Type 2, 26%; Type 1, 3%), history of stroke or other cerebrovascular disease (16%), peripheral vessel disease (33%), or hypertension in males 65 years of age and older (6%). At baseline, 3,421 patients (17%) had LDL-C levels below 100 mg/dL, of whom 953 (5%) had LDL-C levels below 80 mg/dL; 7,068 patients (34%) had levels between 100 and 130 mg/dL; and 10,047 patients (49%) had levels greater than 130 mg/dL.

The HPS results showed that simvastatin 40 mg/day significantly reduced: total and CHD mortality; non-fatal myocardial infarctions, stroke, and revascularization procedures (coronary and non-coronary) (see Table 1).

TABLE 1: Summary of Heart Protection Study Results
Endpoint | Simvastatin(N = 10,269)n (%)† | Placebo (N = 10,267)n (%)† | Risk Reduction (%) (95% CI) | p-Value
Primary
Mortality | 1,328 (12.9) | 1,507 (14.7) | 13(6 to 19) | p = 0.0003
CHD mortality | 587 (5.7) | 707 (6.9) | 18(8 to 26) | p = 0.0005
Secondary
Non-fatal MI | 357 (3.5) | 574 (5.6) | 38(30 to 46) | p <0.0001
Stroke | 444 (4.3) | 585 (5.7) | 25(15 to 34) | p <0.0001
Tertiary
Coronary revascularization | 513 (5) | 725 (7.1) | 30(22 to 38) | p <0.0001
Peripheral and other non-coronary revascularization | 450 (4.4) | 532 (5.2) | 16(5 to 26) | p = 0.006
† n = number of patients with indicated event

Two composite endpoints were defined in order to have sufficient events to assess relative risk reductions across a range of baseline characteristics (see Figure 1). A composite of major coronary events (MCE) was comprised of CHD mortality and non-fatal MI (analyzed by time-to-first event; 898 patients treated with simvastatin had events and 1,212 patients on placebo had events). A composite of major vascular events (MVE) was comprised of MCE, stroke and revascularization procedures including coronary, peripheral and other non-coronary procedures (analyzed by time-to-first event; 2,033 patients treated with simvastatin had events and 2,585 patients on placebo had events). Significant relative risk reductions were observed for both composite endpoints (27% for MCE and 24% for MVE, p <0.0001). Furthermore, treatment with simvastatin produced significant relative risk reductions for all components of the composite endpoints. The risk reductions produced by simvastatin in both MCE and MVE were evident and consistent regardless of cardiovascular disease related medical history at study entry (i.e., CHD alone; or peripheral vascular disease, cerebrovascular disease, diabetes or treated hypertension, with or without CHD), gender, age, creatinine levels up to the entry limit of 2.3 mg/dL, baseline levels of LDL-C, HDL-C, apolipoprotein B and A-1, baseline concomitant cardiovascular medications (i.e., aspirin, beta blockers, or calcium channel blockers), smoking status, alcohol intake, or obesity. Diabetics showed risk reductions for MCE and MVE due to simvastatin treatment regardless of baseline HbA1c levels or obesity with the greatest effects seen for diabetics without CHD.

Figure 1: The Effects of Treatment with Simvastatin on Major Vascular Events and Major Coronary Events in HPS

N = number of patients in each subgroup. The inverted triangles are point estimates of the relative risk, with their 95% confidence intervals represented as a line. The area of a triangle is proportional to the number of patients with MVE or MCE in the subgroup relative to the number with MVE or MCE, respectively, in the entire study population. The vertical solid line represents a relative risk of one. The vertical dashed line represents the point estimate of relative risk in the entire study population.

Angiographic Studies

In the Multicenter Anti-Atheroma Study, the effect of simvastatin on atherosclerosis was assessed by quantitative coronary angiography in hypercholesterolemic patients with coronary heart disease. In this randomized, double-blind, controlled study, patients were treated with simvastatin 20 mg/day or placebo. Angiograms were evaluated at baseline, two and four years. The co-primary study endpoints were mean change per-patient in minimum and mean lumen diameters, indicating focal and diffuse disease, respectively. Simvastatin significantly slowed the progression of lesions as measured in the Year 4 angiogram by both parameters, as well as by change in percent diameter stenosis. In addition, simvastatin significantly decreased the proportion of patients with new lesions and with new total occlusions.

Primary Hypercholesterolemia (Fredrickson type lla and llb)

Simvastatin has been shown to be highly effective in reducing total-C and LDL-C in heterozygous familial and non-familial forms of hypercholesterolemia and in mixed hyperlipidemia. A marked response was seen within 2 weeks, and the maximum therapeutic response occurred within 4 to 6 weeks. The response was maintained during chronic therapy. simvastatin consistently and significantly decreased total-C, LDL-C, total-C/HDL-C ratio, and LDL-C/HDL-C ratio; simvastatin also decreased TG and increased HDL-C (see Table 2).

TABLE 2: Mean Response in Patients with Primary Hypercholesterolemia and Combined (mixed) Hyperlipidemia (Mean Percent Change from Baseline After 6 to 24 Weeks)
TREATMENT | N | TOTAL-C | LDL-C | HDL-C | TG [median percent change]
Lower Dose Comparative Study [mean baseline LDL-C 244 mg/dL and median baseline TG 168 mg/dL] (Mean % Change at Week 6)
Simvastatin5 mg q.p.m. | 109 | -19 | -26 | 10 | -12
Simvastatin10 mg q.p.m. | 110 | -23 | -30 | 12 | -15
Scandinavian Simvastatin Survival Study [mean baseline LDL-C 188 mg/dL and median baseline TG 128 mg/dL] (Mean % Change at Week 6)
Placebo | 2223 | -1 | -1 | 0 | -2
Simvastatin20 mg q.p.m. | 2221 | -28 | -38 | 8 | -19
Upper Dose Comparative Study [mean baseline LDL-C 226 mg/dL and median baseline TG 156 mg/dL] (Mean % Change Averaged atWeeks 18 and 24)
Simvastatin 40 mg q.p.m. | 433 | -31 | -41 | 9 | -18
Simvastatin 80 mg q.p.m. | 664 | -36 | -47 | 8 | -24
Multi-Center Combined Hyperlipidemia Study [mean baseline LDL-C 156 mg/dL and median baseline TG 391 mg/dL] (Mean % Change at Week 6)
Placebo | 125 | 1 | 2 | 3 | -4
Simvastatin 40 mg q.p.m. | 123 | -25 | -29 | 13 | -28
Simvastatin80 mg q.p.m. | 124 | -31 | -36 | 16 | -33

In the Upper Dose Comparative Study, the mean reduction in LDL-C was 47% at the 80 mg dose. Of the 664 patients randomized to 80 mg, 475 patients with plasma TG ≤ 200 mg/dL had a median reduction in TG of 21%, while in 189 patients with TG > 200 mg/dL, the median reduction in TG was 36%. In these studies, patients with TG > 350 mg/dL were excluded.

Hypertriglyceridemia (Fredrickson type lV)

The results of a subgroup analysis in 74 patients with type lV hyperlipidemia from a 130-patient, double-blind, placebo-controlled, 3-period crossover study are presented in Table 3.

TABLE 3: Six-week, Lipid-lowering Effects of Simvastatin in Type lV Hyperlipidemia Median Percent Change (25th and 75th percentile) from Baseline [The median baseline values (mg/dL) for the patients in this study were: total-C = 254, LDL-C = 135, HDL-C = 36, TG = 404, VLDL-C = 83, and non-HDL-C = 215.]
TREATMENT | N | Total-C | LDL-C | HDL-C | TG | VLDL-C | Non-HDL-C
Placebo | 74 | +2(-7, +7) | +1(-8, +14) | +3(-3, +10) | -9(-25, +13) | -7(-25, +11) | +1(-9, +8)
Simvastatin40 mg/day | 74 | -25(-34, -19) | -28(-40, -17) | +11(+5, +23) | -29(-43, -16) | -37(-54, -23) | -32(-42, -23)
80 mg/day | 74 | -32(-38, -24) | -37(-46, -26) | +15(+5, +23) | -34(-45, -18) | -41(-57, -28) | -38(-49, -32)

Dysbetalipoproteinemia (Fredrickson type lll)

The results of a subgroup analysis in 7 patients with type lll hyperlipidemia (dysbetalipoproteinemia) (apo E2/2) (VLDL-C/TG > 0.25) from a 130-patient, double-blind, placebo-controlled, 3-period crossover study are presented in Table 4. In this study the median baseline values (mg/dL) were: total-C = 324, LDL-C = 121, HDL-C = 31, TG = 411, VLDL-C = 170, and non HDL-C = 291.

Table 4: Six-week, Lipid-lowering Effects of Simvastatin in Type lll Hyperlipidemia Median Percent Change (min,max) from Baseline†
TREATMENT | N | Total-C | LDL-C + IDL | HDL-C | TG | VLDL-C+IDL | Non-HDL-C
Placebo | 7 | -8(-24, +34) | -8(-27, +23) | -2(-21, +16) | +4(-22, +90) | -4(-28, +78) | -8(-26, -39)
Simvastatin 40 mg/day | 7 | -50(-66, -39) | -50(-60, -31) | +7(-8, +23) | -41(-74, -16) | -58(-90, -37) | -57(-72, -44)
Simvastatin 80 mg/day | 7 | -52(-55, -41) | -51(-57, -28) | +7(-5, +29) | -38(-58, +2) | -60(-72, -39) | -59(-61, -46)

Homozygous Familial Hypercholesterolemia

In a controlled clinical study, 12 patients 15 to 39 years of age with homozygous familial hypercholesterolemia received simvastatin 40 mg/day in a single dose or in 3 divided doses, or 80 mg/day in 3 divided doses. Eleven of the 12 patients had reductions in LDL-C. In those patients with reductions, the mean LDL-C changes for the 40 and 80 mg doses were 14% (range 8% to 23%, median 12%) and 30% (range 14% to 46%, median 29%), respectively. One patient had an increase of 15% in LDL-C. Another patient with absent LDL-C receptor function had an LDL-C reduction of 41% with the 80 mg dose.

Endocrine Function

In clinical studies, simvastatin did not impair adrenal reserve or significantly reduce basal plasma cortisol concentration. Small reductions from baseline in basal plasma testosterone in men were observed in clinical studies with simvastatin, an effect also observed with other inhibitors of HMG-CoA reductase and the bile acid sequestrant cholestyramine. There was no effect on plasma gonadotropin levels. In a placebo-controlled, 12-week study there was no significant effect of simvastatin 80 mg on the plasma testosterone response to human chorionic gonadotropin (hCG). In another 24-week study, simvastatin 20 to 40 mg had no detectable effect on spermatogenesis. In 4S, in which 4,444 patients were randomized to simvastatin 20 to 40 mg/day or placebo for a median duration of 5.4 years, the incidence of male sexual adverse events in the two treatment groups was not significantly different. Because of these factors, the small changes in plasma testosterone are unlikely to be clinically significant. The effects, if any, on the pituitary-gonadal axis in pre-menopausal women are unknown.

Clinical Studies in Adolescents

In a double-blind, placebo-controlled study, 175 patients (99 adolescent boys and 76 post-menarchal girls) 10 to 17 years of age (mean age 14.1 years) with heterozygous familial hypercholesterolemia (heFH) were randomized to simvastatin (n = 106) or placebo (n = 67) for 24 weeks (base study). Inclusion in the study required a baseline LDL-C level between 160 and 400 mg/dL and at least one parent with an LDL-C level > 189 mg/dL. The dosage of simvastatin (once daily in the evening) was 10 mg for the first 8 weeks, 20 mg for the second 8 weeks, and 40 mg thereafter. In a 24-week extension, 144 patients elected to continue therapy and received simvastatin 40 mg or placebo.

Simvastatin significantly decreased plasma levels of total-C, LDL-C, and Apo B (see Table 5). Results from the extension at 48 weeks were comparable to those observed in the base study.

TABLE 5: Lipid-lowering Effects of Simvastatin in Adolescent Patients with Heterozygous Familial Hypercholesterolemia (Mean Percent Change from Baseline)
Dosage | Duration | N |  | Total-C | LDL-C | HDL-C | TG [median percent change] | Apo B
Placebo | 24 Weeks | 67 | % Change from Baseline(95% CI) | 1.6(-2.2, 5.3) | 1.1(-3.4, 5.5) | 3.6(-0.7, 8) | -3.2(-11.8, 5.4) | -0.5(-4.7, 3.6)
 |  |  | Mean baseline, mg/dL (SD) | 278.6(51.8) | 211.9(49) | 46.9(11.9) | 90(50.7) | 186.3(38.1)
Simvastatin | 24 Weeks | 106 | % Change from Baseline (95% CI) | -26.5(-29.6, -23.3) | -36.8(-40.5, -33) | 8.3(4.6, 1.9) | -7.9(-15.8, 0) | -32.4 (-35.9, -29)
 |  |  | Mean baseline, mg/dL (SD) | 270.2(44) | 203.8(41.5) | 47.7(9) | 78.3(46) | 179.9(33.8)

After 24 weeks of treatment, the mean achieved LDL-C value was 124.9 mg/dL (range: 64to 289 mg/dL) in the simvastatin 40 mg group compared to 207.8 mg/dL (range: 128 to 334mg/dL) in the placebo group.

The safety and efficacy of doses above 40 mg daily have not been studied in children with heterozygous familial hypercholesterolemia. The long-term efficacy of simvastatin therapy in childhood to reduce morbidity and mortality in adulthood has not been established.

INDICATIONS AND USAGE

Lipid-altering agents should be used in addition to a diet restricted in saturated fat and cholesterol (see National Cholesterol Education Program [NCEP] Treatment Guidelines, below).

In patients with CHD or at high risk of CHD, simvastatin can be started simultaneously with diet.

Reductions in Risk of CHD Mortality and Cardiovascular Events

In patients at high risk of coronary events because of existing coronary heart disease, diabetes, peripheral vessel disease, history of stroke or other cerebrovascular disease, simvastatin is indicated to:

- Reduce the risk of total mortality by reducing CHD deaths.
- Reduce the risk of non-fatal myocardial infarction and stroke.
- Reduce the need for coronary and non-coronary revascularization procedures.

Patients with Hypercholesterolemia Requiring Modifications of Lipid Profiles

Simvastatin tablets are indicated to:

- Reduce elevated total-C, LDL-C, Apo B, and TG, and to increase HDL-C in patients with primary hypercholesterolemia (heterozygous familial and nonfamilial) and mixed dyslipidemia (Fredrickson types IIa and IIb).
- Treat patients with hypertriglyceridemia (Fredrickson type lV hyperlipidemia).
- Treat patients with primary dysbetalipoproteinemia (Fredrickson type lll hyperlipidemia).
- Reduce total-C and LDL-C in patients with homozygous familial hypercholesterolemia as an adjunct to other lipid-lowering treatments (e.g., LDL apheresis) or if such treatments are unavailable.

Adolescent Patients with Heterozygous Familial Hypercholesterolemia (HeFH)

Simvastatin tablets are indicated as an adjunct to diet to reduce total-C, LDL-C, and Apo B levels in adolescent boys and girls who are at least one year post-menarche, 10 to 17 years of age, with heterozygous familial hypercholesterolemia, if after an adequate trial of diet therapy the following findings are present:

1. LDL cholesterol remains ≥ 190 mg/dL; or
2. LDL cholesterol remains ≥ 160 mg/dL and

- There is a positive family history of premature cardiovascular disease (CVD) or
- Two or more other CVD risk factors are present in the adolescent patient.

The minimum goal of treatment in pediatric and adolescent patients is to achieve a mean LDL-C < 130 mg/dL. The optimal age at which to initiate lipid-lowering therapy to decrease the risk of symptomatic adulthood CAD has not been determined.

General Recommendations

Prior to initiating therapy with simvastatin tablets, secondary causes for hypercholesterolemia (e.g., hypothyroidism, nephrotic syndrome, dysproteinemias, obstructive liver disease, other drug therapy, alcoholism) should be excluded, and a lipid profile performed to measure total-C, HDL-C, and TG. For patients with TG less than 400 mg/dL (< 4.5 mmol/L), LDL-C can be estimated using the following equation:

LDL-C = total-C – [(0.20 x TG) + HDL-C]

For TG levels > 400 mg/dL (> 4.5 mmol/L), this equation is less accurate and LDL-C concentrations should be determined by ultracentrifugation. In many hypertriglyceridemic patients, LDL-C may be low or normal despite elevated total-C. In such cases, simvastatin tablets are not indicated.

Lipid determinations should be performed at intervals of no less than four weeks and dosage adjusted according to the patient's response to therapy.

The NCEP Treatment Guidelines are summarized in Table 6:

TABLE 6: NCEP Treatment Guidelines: LDL-C Goals and Cutpoints for Therapeutic Lifestyle Changes and Drug Therapy in Different Risk Categories
Risk Category | LDL Goal (mg/dL) | LDL Level at Which to Initiate Therapeutic Lifestyle Changes (mg/dL) | LDL Level at Which to Consider Drug Therapy (mg/dL)
CHD [CHD, coronary heart disease] orCHD risk equivalents (10-year risk > 20%) | < 100 | ≥ 100 | ≥ 130 (100 to 129: drug optional)S [ome authorities recommend use of LDL-lowering drugs in this category if an LDL-C level of <100 mg/dL cannot be achieved by therapeutic lifestyle changes. Others prefer use of drugs that primarily modify triglycerides and HDL-C, e.g., nicotinic acid or fibrate. Clinical judgment also may call for deferring drug therapy in this subcategory.]
2+ Risk factors (10-year risk ≤ 20%) | < 130 | ≥ 130 | 10-year risk 10 to 20%: ≥ 130 10-year risk <10%: ≥ 160
0 to 1 Risk factor [Almost all people with 0-1 risk factor have a 10-year risk <10%; thus, 10-year risk assessment in people with 0-1 risk factor is not necessary.] | < 160 | ≥ 160 | ≥ 190 (160 to 189: LDL-lowering drug optional)

After the LDL-C goal has been achieved, if the TG is still ≥ 200 mg/dL, non-HDL-C (total-C minus HDL-C) becomes a secondary target of therapy. Non-HDL-C goals are set 30 mg/dL higher than LDL-C goals for each risk category.

At the time of hospitalization for an acute coronary event, consideration can be given to initiating drug therapy at discharge.

The NCEP classification of cholesterol levels in pediatric patients with a familial history of either hypercholesterolemia or premature cardiovascular disease is summarized in Table 7.

TABLE 7: NCEP Classification of Cholesterol Levels in Pediatric Patients with a Familial History of Either HeFH or Premature CVD
Category | Total-C (mg/dL) | LDL-C (mg/dL)
Acceptable | <170 | < 110
Borderline | 170 to 199 | 110 to 129
High | ≥ 200 | ≥ 130

Since the goal of treatment is to lower LDL-C, the NCEP recommends that LDL-C levels be used to initiate and assess treatment response. Only if LDL-C levels are not available, should the total-C be used to monitor therapy.

Simvastatin is indicated to reduce elevated LDL-C and TG levels in patients with Type IIb hyperlipidemia (where hypercholesterolemia is the major abnormality). However, it has not been studied in conditions where the major abnormality is elevation of chylomicrons (i.e., hyperlipidemia Fredrickson types I and V)^3.

CONTRAINDICATIONS

Hypersensitivity to any component of this medication.

Active liver disease or unexplained persistent elevations of serum transaminases (see WARNINGS).

Pregnancy and lactation. Atherosclerosis is a chronic process and the discontinuation of lipid-lowering drugs during pregnancy should have little impact on the outcome of long-term therapy of primary hypercholesterolemia. Moreover, cholesterol and other products of the cholesterol biosynthesis pathway are essential components for fetal development, including synthesis of steroids and cell membranes. Because of the ability of inhibitors of HMG-CoA reductase such as simvastatin to decrease the synthesis of cholesterol and possibly other products of the cholesterol biosynthesis pathway, simvastatin is contraindicated during pregnancy and in nursing mothers. Simvastatin should be administered to women of childbearing age only when such patients are highly unlikely to conceive. If the patient becomes pregnant while taking this drug, simvastatin should be discontinued immediately and the patient should be apprised of the potential hazard to the fetus (see PRECAUTIONS, Pregnancy).

WARNINGS

Myopathy/Rhabdomyolysis

Simvastatin, like other inhibitors of HMG-CoA reductase, occasionally causes myopathy manifested as muscle pain, tenderness or weakness with creatine kinase (CK) above ten times the upper limit of normal (ULN). Myopathy sometimes takes the form of rhabdomyolysis with or without acute renal failure secondary to myoglobinuria, and rare fatalities have occurred. The risk of myopathy is increased by high levels of HMG-CoA reductase inhibitory activity in plasma.

As with other HMG-CoA reductase inhibitors, the risk of myopathy/rhabdomyolysis is dose related. In a clinical trial database in which 41,050 patients were treated with simvastatin with 24,747 (approximately 60%) treated for at least 4 years, the incidence of myopathy was approximately 0.02%, 0.08% and 0.53% at 20, 40 and 80 mg/day, respectively. In these trials, patients were carefully monitored and some interacting medicinal products were excluded.

All patients starting therapy with simvastatin or whose dose of simvastatin is being increased, should be advised of the risk of myopathy and told to report promptly any unexplained muscle pain, tenderness or weakness. Simvastatin therapy should be discontinued immediately if myopathy is diagnosed or suspected. In most cases, muscle symptoms and CK increases resolved when treatment was promptly discontinued. Periodic CK determinations may be considered in patients starting therapy with simvastatin or whose dose is being increased, but there is no assurance that such monitoring will prevent myopathy.

Many of the patients who have developed rhabdomyolysis on therapy with simvastatin have had complicated medical histories, including renal insufficiency usually as a consequence of long-standing diabetes mellitus. Such patients merit closer monitoring. Therapy with simvastatin should be temporarily stopped a few days prior to elective major surgery and when any major medical or surgical condition supervenes.

The risk of myopathy/rhabdomyolysis is increased by concomitant use of simvastatin with the following:

Potent inhibitors of CYP3A4: Simvastatin, like several other inhibitors of HMG-CoA reductase, is a substrate of cytochrome P450 3A4 (CYP3A4). When simvastatin is used with a potent inhibitor of CYP3A4, elevated plasma levels of HMG-CoA reductase inhibitory activity can increase the risk of myopathy and rhabdomyolysis, particularly with higher doses of simvastatin.

The use of simvastatin concomitantly with the potent CYP3A4 inhibitors itraconazole, ketoconazole, erythromycin, clarithromycin, telithromycin, HIV protease inhibitors, nefazodone, or large quantities of grapefruit juice (> 1 quart daily) should be avoided. Concomitant use of other medicines labeled as having a potent inhibitory effect on CYP3A4 should be avoided unless the benefits of combined therapy outweigh the increased risk. If treatment with itraconazole, ketoconazole, erythromycin, clarithromycin or telithromycin is unavoidable, therapy with simvastatin should be suspended during the course of treatment.

Gemfibrozil, particularly with higher doses of simvastatin: The dose of simvastatin should not exceed 10 mg daily in patients receiving concomitant medication with gemfibrozil. The combined use of simvastatin with gemfibrozil should be avoided, unless the benefits are likely to outweigh the increased risks of this drug combination.

Other lipid-lowering drugs (other fibrates or ≥ 1 g/day of niacin): Caution should be used when prescribing other fibrates or lipid-lowering doses (≥ 1 g/day) of niacin with simvastatin, as these agents can cause myopathy when given alone. The benefit of further alterations in lipid levels by the combined use of simvastatin with other fibrates or niacin should be carefully weighed against the potential risks of these combinations.

Cyclosporine or danazol, with higher doses of simvastatin: The dose of simvastatin should not exceed 10 mg daily in patients receiving concomitant medication with cyclosporine or danazol. The benefits of the use of simvastatin in patients receiving cyclosporine or danazol should be carefully weighed against the risks of these combinations.

Amiodarone or verapamil, with higher doses of simvastatin: The dose of simvastatin should not exceed 20 mg daily in patients receiving concomitant medication with amiodarone or verapamil. The combined use of simvastatin at doses higher than 20 mg daily with amiodarone or verapamil should be avoided unless the clinical benefit is likely to outweigh the increased risk of myopathy. In an ongoing clinical trial, myopathy has been reported in 6% of patients receiving simvastatin 80 mg and amiodarone. In an analysis of clinical trials involving 25,248 patients treated with simvastatin 20 to 80 mg, the incidence of myopathy was higher in patients receiving verapamil and simvastatin (4/635; 0.63%) than in patients taking simvastatin without a calcium channel blocker (13/21,224; 0.061%).

Prescribing recommendations for interacting agents are summarized in Table 8 (see also CLINICAL PHARMACOLOGY, Pharmacokinetics; PRECAUTIONS, Drug Interactions; DOSAGE AND ADMINISTRATION).

TABLE 8: Drug Interactions Associated with Increased Risk of Myopathy/Rhabdomyolysis
Interacting Agents | Prescribing Recommendations
Itraconazole | Avoid simvastatin
Ketoconazole
Erythromycin
Clarithromycin
Telithromycin
HIV protease inhibitors
Nefazodone
Gemfibrozil | Do not exceed 10 mg simvastatin daily
Cyclosporine
Danazol
Amiodarone | Do not exceed 20 mg simvastatin daily
Verapamil
Grapefruit juice | Avoid large quantities of grapefruit juice (> 1 quart daily)

Liver Dysfunction

Persistent increases (to more than 3X the ULN) in serum transaminases have occurred in approximately 1% of patients who received simvastatin in clinical studies. When drug treatment was interrupted or discontinued in these patients, the transaminase levels usually fell slowly to pretreatment levels. The increases were not associated with jaundice or other clinical signs or symptoms. There was no evidence of hypersensitivity.

In 4S (see CLINICAL PHARMACOLOGY, Clinical Studies), the number of patients with more than one transaminase elevation to > 3X ULN, over the course of the study, was not significantly different between the simvastatin and placebo groups (14 [0.7%] vs. 12 [0.6%]). Elevated transaminases resulted in the discontinuation of 8 patients from therapy in the simvastatin group (n = 2,221) and 5 in the placebo group (n = 2,223). Of the 1,986 simvastatin treated patients in 4S with normal liver function tests (LFTs) at baseline, only 8 (0.4%) developed consecutive LFT elevations to > 3X ULN and/or were discontinued due to transaminase elevations during the 5.4 years (median follow-up) of the study. Among these 8 patients, 5 initially developed these abnormalities within the first year. All of the patients in this study received a starting dose of 20 mg of simvastatin; 37% were titrated to 40 mg.

In 2 controlled clinical studies in 1,105 patients, the 12 month incidence of persistent hepatic transaminase elevation without regard to drug relationship was 0.9% and 2.1% at the 40 and 80 mg dose, respectively. No patients developed persistent liver function abnormalities following the initial 6 months of treatment at a given dose.

It is recommended that liver function tests be performed before the initiation of treatment, and thereafter when clinically indicated. Patients titrated to the 80 mg dose should receive an additional test prior to titration, 3 months after titration to the 80 mg dose, and periodically thereafter (e.g., semiannually) for the first year of treatment. Patients who develop increased transaminase levels should be monitored with a second liver function evaluation to confirm the finding and be followed thereafter with frequent liver function tests until the abnormality(ies) return to normal. Should an increase in AST or ALT of 3X ULN or greater persist, withdrawal of therapy with simvastatin is recommended.

The drug should be used with caution in patients who consume substantial quantities of alcohol and/or have a past history of liver disease. Active liver diseases or unexplained transaminase elevations are contraindications to the use of simvastatin.

As with other lipid-lowering agents, moderate (less than 3X ULN) elevations of serum transaminases have been reported following therapy with simvastatin. These changes appeared soon after initiation of therapy with simvastatin, were often transient, were not accompanied by any symptoms and did not require interruption of treatment.

PRECAUTIONS

General

Simvastatin may cause elevation of CK and transaminase levels (see WARNINGS and ADVERSE REACTIONS). This should be considered in the differential diagnosis of chest pain in a patient on therapy with simvastatin.

Information for Patients

Patients should be advised about substances they should not take concomitantly with simvastatin and be advised to report promptly unexplained muscle pain, tenderness, or weakness (see list below and WARNINGS, Myopathy/Rhabdomyolysis). Patients should also be advised to inform other physicians prescribing a new medication that they are taking simvastatin.

CYP3A4 Interactions

Simvastatin is metabolized by CYP3A4 but has no CYP3A4 inhibitory activity; therefore it is not expected to affect the plasma concentrations of other drugs metabolized by CYP3A4. Potent inhibitors of CYP3A4 (below) increase the risk of myopathy by reducing the elimination of simvastatin.

See WARNINGS, Myopathy/Rhabdomyolysis, and CLINICAL PHARMACOLOGY, Pharmacokinetics.

Itraconazole

Ketoconazole

Erythromycin

Clarithromycin

Telithromycin

HIV protease inhibitors

Nefazodone

Large quantities of grapefruit juice (>1 quart daily)

Interactions with lipid-lowering drugs that can cause myopathy when given alone

See WARNINGS, Myopathy/Rhabdomyolysis.

The risk of myopathy is increased by gemfibrozil (see DOSAGE AND ADMINISTRATION) and to a lesser extent by other fibrates and niacin (nicotinic acid) (≥ 1 g/day).

Other drug interactions

Cyclosporine or Danazol: The risk of myopathy/rhabdomyolysis is increased by concomitant administration of cyclosporine or danazol particularly with higher doses of simvastatin (see CLINICAL PHARMACOLOGY,Pharmacokinetics; WARNINGS, Myopathy/Rhabdomyolysis).

Amiodarone or Verapamil: The risk of myopathy/rhabdomyolysis is increased by concomitant administration of amiodarone or verapamil with higher doses of simvastatin (see WARNINGS, Myopathy/Rhabdomyolysis).

Propranolol: In healthy male volunteers there was a significant decrease in mean Cmax, but no change in AUC, for simvastatin total and active inhibitors with concomitant administration of single doses of simvastatin and propranolol. The clinical relevance of this finding is unclear. The pharmacokinetics of the enantiomers of propranolol were not affected.

Digoxin: Concomitant administration of a single dose of digoxin in healthy male volunteers receiving simvastatin resulted in a slight elevation (less than 0.3 ng/mL) in digoxin concentrations in plasma (as measured by a radioimmunoassay) compared to concomitant administration of placebo and digoxin. Patients taking digoxin should be monitored appropriately when simvastatin is initiated.

Warfarin: In two clinical studies, one in normal volunteers and the other in hypercholesterolemic patients, simvastatin 20, 40 mg/day modestly potentiated the effect of coumarin anticoagulants: the prothrombin time, reported as International Normalized Ratio (INR), increased from a baseline of 1.7 to 1.8 and from 2.6 to 3.4 in the volunteer and patient studies, respectively. With other reductase inhibitors, clinically evident bleeding and/or increased prothrombin time has been reported in a few patients taking coumarin anticoagulants concomitantly. In such patients, prothrombin time should be determined before starting simvastatin and frequently enough during early therapy to ensure that no significant alteration of prothrombin time occurs. Once a stable prothrombin time has been documented, prothrombin times can be monitored at the intervals usually recommended for patients on coumarin anticoagulants. If the dose of simvastatin is changed or discontinued, the same procedure should be repeated. Simvastatin therapy has not been associated with bleeding or with changes in prothrombin time in patients not taking anticoagulants.

CNS Toxicity

Optic nerve degeneration was seen in clinically normal dogs treated with simvastatin for 14 weeks at 180 mg/kg/day, a dose that produced mean plasma drug levels about 12 times higher than the mean plasma drug level in humans taking 80 mg/day.

A chemically similar drug in this class also produced optic nerve degeneration (Wallerian degeneration of retinogeniculate fibers) in clinically normal dogs in a dose-dependent fashion starting at 60 mg/kg/day, a dose that produced mean plasma drug levels about 30 times higher than the mean plasma drug level in humans taking the highest recommended dose (as measured by total enzyme inhibitory activity). This same drug also produced vestibulocochlear Wallerian-like degeneration and retinal ganglion cell chromatolysis in dogs treated for 14 weeks at 180 mg/kg/day, a dose that resulted in a mean plasma drug level similar to that seen with the 60 mg/kg/day dose.

CNS vascular lesions, characterized by perivascular hemorrhage and edema, mononuclear cell infiltration of perivascular spaces, perivascular fibrin deposits and necrosis of small vessels were seen in dogs treated with simvastatin at a dose of 360 mg/kg/day, a dose that produced mean plasma drug levels that were about 14 times higher than the mean plasma drug levels in humans taking 80 mg/day. Similar CNS vascular lesions have been observed with several other drugs of this class.

There were cataracts in female rats after two years of treatment with 50 and 100 mg/kg/day (22 and 25 times the human AUC at 80 mg/day, respectively) and in dogs after three months at 90 mg/kg/day (19 times) and at two years at 50 mg/kg/day (5 times).

Carcinogenesis, Mutagenesis, Impairment of Fertility

In a 72-week carcinogenicity study, mice were administered daily doses of simvastatin of 25, 100, and 400 mg/kg body weight, which resulted in mean plasma drug levels approximately 1, 4, and 8 times higher than the mean human plasma drug level, respectively (as total inhibitory activity based on AUC) after an 80 mg oral dose. Liver carcinomas were significantly increased in high-dose females and mid- and high-dose males with a maximum incidence of 90% in males. The incidence of adenomas of the liver was significantly increased in mid- and high-dose females. Drug treatment also significantly increased the incidence of lung adenomas in mid- and high-dose males and females. Adenomas of the Harderian gland (a gland of the eye of rodents) were significantly higher in high-dose mice than in controls. No evidence of a tumorigenic effect was observed at 25 mg/kg/day.

In a separate 92-week carcinogenicity study in mice at doses up to 25 mg/kg/day, no evidence of a tumorigenic effect was observed (mean plasma drug levels were 1 times higher than humans given 80 mg simvastatin as measured by AUC).

In a two-year study in rats at 25 mg/kg/day, there was a statistically significant increase in the incidence of thyroid follicular adenomas in female rats exposed to approximately 11 times higher levels of simvastatin than in humans given 80 mg simvastatin (as measured by AUC).

A second two-year rat carcinogenicity study with doses of 50 and 100 mg/kg/day produced hepatocellular adenomas and carcinomas (in female rats at both doses and in males at 100 mg/kg/day). Thyroid follicular cell adenomas were increased in males and females at both doses; thyroid follicular cell carcinomas were increased in females at 100 mg/kg/day. The increased incidence of thyroid neoplasms appears to be consistent with findings from other HMG-CoA reductase inhibitors. These treatment levels represented plasma drug levels (AUC) of approximately 7 and 15 times (males) and 22 and 25 times (females) the mean human plasma drug exposure after an 80 milligram daily dose.

No evidence of mutagenicity was observed in a microbial mutagenicity (Ames) test with or without rat or mouse liver metabolic activation. In addition, no evidence of damage to genetic material was noted in an in vitro alkaline elution assay using rat hepatocytes, a V-79 mammalian cell forward mutation study, an in vitro chromosome aberration study in CHO cells, or an in vivo chromosomal aberration assay in mouse bone marrow.

There was decreased fertility in male rats treated with simvastatin for 34 weeks at 25 mg/kg body weight (4 times the maximum human exposure level, based on AUC, in patients receiving 80 mg/day); however, this effect was not observed during a subsequent fertility study in which simvastatin was administered at this same dose level to male rats for 11 weeks (the entire cycle of spermatogenesis including epididymal maturation). No microscopic changes were observed in the testes of rats from either study. At 180 mg/kg/day, (which produces exposure levels 22 times higher than those in humans taking 80 mg/day based on surface area, mg/m^2), seminiferous tubule degeneration (necrosis and loss of spermatogenic epithelium) was observed. In dogs, there was drug-related testicular atrophy, decreased spermatogenesis, spermatocytic degeneration and giant cell formation at 10 mg/kg/day, (approximately 2 times the human exposure, based on AUC, at 80 mg/day). The clinical significance of these findings is unclear.

Pregnancy

Pregnancy Category X

See CONTRAINDICATIONS.

Safety in pregnant women has not been established.

Simvastatin was not teratogenic in rats at doses of 25 mg/kg/day or in rabbits at doses up to 10 mg/kg daily. These doses resulted in 3 times (rat) or 3 times (rabbit) the human exposure based on mg/m2 surface area. However, in studies with another structurally-related HMG-CoA reductase inhibitor, skeletal malformations were observed in rats and mice.

Rare reports of congenital anomalies have been received following intrauterine exposure to HMG-CoA reductase inhibitors. In a review [Manson, J.M., Freyssinges, C., Ducrocq, M.B., Stephenson, W.P., Postmarketing Surveillance of Lovastatin and Simvastatin Exposure During Pregnancy, Reproductive Toxicology, 10(6):439 446, 1996] of approximately 100 prospectively followed pregnancies in women exposed to simvastatin or another structurally related HMG-CoA reductase inhibitor, the incidences of congenital anomalies, spontaneous abortions and fetal deaths/stillbirths did not exceed what would be expected in the general population. The number of cases is adequate only to exclude a 3- to 4-fold increase in congenital anomalies over the background incidence. In 89% of the prospectively followed pregnancies, drug treatment was initiated prior to pregnancy and was discontinued at some point in the first trimester when pregnancy was identified. As safety in pregnant women has not been established and there is no apparent benefit to therapy with simvastatin during pregnancy (see CONTRAINDICATIONS), treatment should be immediately discontinued as soon as pregnancy is recognized. Simvastatin should be administered to women of child-bearing potential only when such patients are highly unlikely to conceive and have been informed of the potential hazards.

Nursing Mothers

It is not known whether simvastatin is excreted in human milk. Because a small amount of another drug in this class is excreted in human milk and because of the potential for serious adverse reactions in nursing infants, women taking simvastatin should not nurse their infants (see CONTRAINDICATIONS).

Pediatric Use

Safety and effectiveness of simvastatin in patients 10 to 17 years of age with heterozygous familial hypercholesterolemia have been evaluated in a controlled clinical trial in adolescent boys and in girls who were at least 1 year post-menarche. Patients treated with simvastatin had an adverse experience profile generally similar to that of patients treated with placebo. Doses greater than 40 mg have not been studied in this population. In this limited controlled study, there was no detectable effect on growth or sexual maturation in the adolescent boys or girls, or any effect on menstrual cycle length in girls. See CLINICAL PHARMACOLOGY, Clinical Studies in Adolescents; ADVERSE REACTIONS, Adolescent Patients; and DOSAGE AND ADMINISTRATION, Adolescents (10 to 17 years of age) with Heterozygous Familial Hypercholesterolemia. Adolescent females should be counseled on appropriate contraceptive methods while on simvastatin therapy (see CONTRAINDICATIONS and PRECAUTIONS, Pregnancy). Simvastatin has not been studied in patients younger than 10 years of age, nor in pre-menarchal girls.

Geriatric Use

A pharmacokinetic study with simvastatin showed the mean plasma level of HMG-CoA reductase inhibitory activity to be approximately 45% higher in elderly patients between 70 to 78 years of age compared with patients between 18 to 30 years of age. In 4S, 1,021 (23%) of 4,444 patients were 65 or older. In 4S, lipid-lowering efficacy was at least as great in elderly patients compared with younger patients. In this study, smvastatin significantly reduced total mortality and CHD mortality in elderly patients with a history of CHD. In HPS, 52% of patients were elderly (4,891 patients 65 to 69 years and 5,806 patients 70 years or older). The relative risk reductions of CHD death, non-fatal MI, coronary and non-coronary revascularization procedures, and stroke were similar in older and younger patients (see CLINICAL PHARMACOLOGY). In HPS, among 32,145 patients entering the active run-in period, there were 2 cases of myopathy/rhabdomyolysis; these patients were aged 67 and 73. Of the 7 cases of myopathy/rhabdomyolysis among 10,269 patients allocated to simvastatin, 4 were aged 65 or more (at baseline), of whom one was over 75. There were no overall differences in safety between older and younger patients in either 4S or HPS.

ADVERSE REACTIONS

In the pre-marketing controlled clinical studies and their open extensions (2,423 patients with mean duration of follow-up of approximately 18 months), 1.4% of patients were discontinued due to adverse experiences attributable to simvastatin. Adverse reactions have usually been mild and transient. simvastatin has been evaluated for serious adverse reactions in more than 21,000 patients and is generally well tolerated.

In Adults

Adverse experiences occurring in adults at an incidence of 1% or greater in patients treated with simvastatin, regardless of causality, in controlled clinical studies are shown in Table 9.

TABLE 9: Adverse Experiences in Clinical Studies Incidence 1 Percent or Greater, Regardless of Causality
 | Simvastatin(N = 1,583)% | Placebo(N = 157)% | Cholestyramine(N = 179)%
Body as a Whole
Abdominal pain | 3.2 | 3.2 | 8.9
Asthenia | 1.6 | 2.5 | 1.1
Gastrointestinal
Constipation | 2.3 | 1.3 | 29.1
Diarrhea | 1.9 | 2.5 | 7.8
Dyspepsia | 1.1 | — | 4.5
Flatulence | 1.9 | 1.3 | 14.5
Nausea | 1.3 | 1.9 | 10.1
Nervous System/ Psychiatric
Headache | 3.5 | 5.1 | 4.5
Respiratory
Upper respiratory infection | 2.1 | 1.9 | 3.4

Clinical Adverse Experiences

In 4S (see CLINICAL PHARMACOLOGY, Clinical Studies) involving 4,444 patients treated with 20 to 40 mg/day of simvastatin (n = 2,221) or placebo (n = 2,223), the safety and tolerability profiles were comparable between groups over the median 5.4 years of the study. The clinical adverse experiences reported as possibly, probably, or definitely drug-related in ≥ 0.5% in either treatment group are shown in Table 10.

TABLE 10: Drug-Related Clinical Adverse Experiences in 4S Incidence 0.5 Percent or Greater
 | Simvastatin (N = 2,221)% | Placebo(N = 2,223)%
Body as a Whole
Abdominal pain | 0.9 | 0.9
Gastrointestinal
Diarrhea | 0.5 | 0.3
Dyspepsia | 0.6 | 0.5
Flatulence | 0.9 | 0.7
Nausea | 0.4 | 0.6
Musculoskeletal
Myalgia | 1.2 | 1.3
Skin
Eczema | 0.8 | 0.8
Pruritus | 0.5 | 0.4
Rash | 0.6 | 0.6
Special Senses
Cataract | 0.5 | 0.8

Clinical Adverse Experiences

In HPS (see CLINICAL PHARMACOLOGY, Clinical Studies), involving 20,536 patients treated with simvastatin 40 mg/day (n = 10,269) or placebo (n = 10,267), the safety profiles were comparable between patients treated with simvastatin and patients treated with placebo over the mean 5 years of the study. In this large trial, only serious adverse events and discontinuations due to any adverse events were recorded. Discontinuation rates due to adverse experiences were comparable (4.8% in patients treated with simvastatin compared with 5.1% in patients treated with placebo). The incidence of myopathy/rhabdomyolysis was < 0.1% in patients treated with simvastatin .

The following effects have been reported with drugs in this class. Not all the effects listed below have necessarily been associated with simvastatin therapy.

Skeletal : muscle cramps, myalgia, myopathy, rhabdomyolysis, arthralgias.

Neurological: dysfunction of certain cranial nerves (including alteration of taste, impairment of extra-ocular movement, facial paresis), tremor, dizziness, vertigo, memory loss, paresthesia, peripheral neuropathy, peripheral nerve palsy, psychic disturbances, anxiety, insomnia, depression.

Hypersensitivity Reactions: An apparent hypersensitivity syndrome has been reported rarely which has included one or more of the following features: anaphylaxis, angioedema, lupus erythematous-like syndrome, polymyalgia rheumatica, dermatomyositis, vasculitis, purpura, thrombocytopenia, leukopenia, hemolytic anemia, positive ANA, ESR increase, eosinophilia, arthritis, arthralgia, urticaria, asthenia, photosensitivity, fever, chills, flushing, malaise, dyspnea, toxic epidermal necrolysis, erythema multiforme, including Stevens-Johnson syndrome.

Gastrointestinal: pancreatitis, hepatitis, including chronic active hepatitis, cholestatic jaundice, fatty change in liver, and, rarely, cirrhosis, fulminant hepatic necrosis, and hepatoma; anorexia, vomiting.

Skin: alopecia, pruritus. A variety of skin changes (e.g., nodules, discoloration, dryness of skin/mucous membranes, changes to hair/nails) have been reported.

Reproductive: gynecomastia, loss of libido, erectile dysfunction.

Eye: progression of cataracts (lens opacities), ophthalmoplegia.

Laboratory Abnormalities: elevated transaminases, alkaline phosphatase, γ glutamyl transpeptidase, and bilirubin; thyroid function abnormalities.

Laboratory Tests

Marked persistent increases of serum transaminases have been noted (see WARNINGS, Liver Dysfunction). About 5% of patients had elevations of CK levels of 3 or more times the normal value on one or more occasions. This was attributable to the noncardiac fraction of CK. Muscle pain or dysfunction usually was not reported (see WARNINGS, Myopathy/Rhabdomyolysis).

Concomitant Lipid-Lowering Therapy

In controlled clinical studies in which simvastatin was administered concomitantly with cholestyramine, no adverse reactions peculiar to this concomitant treatment were observed. The adverse reactions that occurred were limited to those reported previously with simvastatin or cholestyramine. The combined use of simvastatin at doses exceeding 10 mg/day with gemfibrozil should be avoided (see WARNINGS, Myopathy/Rhabdomyolysis).

Adolescent Patients (ages 10 to 17 years)

In a 48-week, controlled study in adolescent boys and girls who were at least 1 year post-menarche, 10 to 17 years of age with heterozygous familial hypercholesterolemia (n = 175), the safety and tolerability profile of the group treated with simvastatin (10 to 40 mg daily) was generally similar to that of the group treated with placebo, with the most common adverse experiences observed in both groups being upper respiratory infection, headache, abdominal pain, and nausea (see CLINICAL PHARMACOLOGY, Clinical Studies in Adolescents, and PRECAUTIONS, Pediatric Use).

OVERDOSAGE

Significant lethality was observed in mice after a single oral dose of 9 g/m^2. No evidence of lethality was observed in rats or dogs treated with doses of 30 and 100 g/m^2, respectively. No specific diagnostic signs were observed in rodents. At these doses the only signs seen in dogs were emesis and mucoid stools.

A few cases of overdosage with simvastatin have been reported; the maximum dose taken was 3.6 g. All patients recovered without sequelae. Until further experience is obtained, no specific treatment of overdosage with simvastatin can be recommended.

The dialyzability of simvastatin and its metabolites in man is not known at present.

DOSAGE AND ADMINISTRATION

The patient should be placed on a standard cholesterol-lowering diet. In patients with CHD or at high risk of CHD, simvastatin can be started simultaneously with diet. The dosage should be individualized according to the goals of therapy and the patient’s response. (For the treatment of adult dyslipidemia, see NCEP Treatment Guidelines. For the reduction in risks of major coronary events, see CLINICAL PHARMACOLOGY, Clinical Studies in Adults.) The dosage range is 5-80 mg/day (see below).

The recommended usual starting dose is 20 to 40 mg once a day in the evening. For patients at high risk for a CHD event due to existing coronary heart disease, diabetes, peripheral vessel disease, history of stroke or other cerebrovascular disease, the recommended starting dose is 40 mg/day. Lipid determinations should be performed after 4 weeks of therapy and periodically thereafter. See below for dosage recommendations in special populations (i.e., homozygous familial hypercholesterolemia, adolescents and renal insufficiency) or for patients receiving concomitant therapy (i.e., cyclosporine, danazol, amiodarone, verapamil, or gemfibrozil).

Patients with Homozygous Familial Hypercholesterolemia

The recommended dosage for patients with homozygous familial hypercholesterolemia is simvastatin 40 mg/day in the evening or 80 mg/day in 3 divided doses of 20 mg, 20 mg, and an evening dose of 40 mg. Simvastatin should be used as an adjunct to other lipid-lowering treatments (e.g., LDL apheresis) in these patients or if such treatments are unavailable.

Adolescents (10 to 17 years of age) with Heterozygous Familial Hypercholesterolemia

The recommended usual starting dose is 10 mg once a day in the evening. The recommended dosing range is 10 to 40 mg/day; the maximum recommended dose is 40 mg/day. Doses should be individualized according to the recommended goal of therapy (see NCEP Pediatric Panel Guidelines [National Cholesterol Education Program (NCEP): Highlights of the Report of the Expert Panel on Blood Cholesterol Levels in Children and Adolescents. Pediatrics. 89(3):495-501. 1992.] and CLINICAL PHARMACOLOGY). Adjustments should be made at intervals of 4 weeks or more.

Concomitant Lipid–Lowering Therapy

Simvastatin is effective alone or when used concomitantly with bile-acid sequestrants. If simvastatin is used in combination with gemfibrozil, the dose of simvastatin should not exceed 10 mg/day (see WARNINGS, Myopathy/Rhabdomyolysis and PRECAUTIONS, Drug Interactions).

Patients taking Cyclosporine or Danazol

In patients taking cyclosporine or danazol concomitantly with simvastatin (see WARNINGS, Myopathy/Rhabdomyolysis), therapy should begin with 5 mg/day and should not exceed 10 mg/day.

Patients taking Amiodarone or Verapamil

In patients taking amiodarone or verapamil concomitantly with simvastatin, the dose should not exceed 20 mg/day (see WARNINGS, Myopathy/Rhabdomyolysis and PRECAUTIONS, Drug Interactions, Other drug interactions).

Patients with Renal Insufficiency

Because simvastatin does not undergo significant renal excretion, modification of dosage should not be necessary in patients with mild to moderate renal insufficiency. However, caution should be exercised when simvastatin is administered to patients with severe renal insufficiency; such patients should be started at 5 mg/day and be closely monitored (see CLINICAL PHARMACOLOGY, Pharmacokinetics and WARNINGS, Myopathy/Rhabdomyolysis).

HOW SUPPLIED

Simvastatin Tablets 5 mg are peach colored, round, film-coated tablets, debossed RX6 on one side and plain on the other side.

Simvastatin Tablets 10 mg are peach colored, round, film-coated tablets, debossed RX790 on one side and plain on the other side.

Simvastatin Tablets 20 mg are tan colored, round, film-coated tablets, debossed RX791 on one side and plain on the other side.

Simvastatin Tablets 40 mg are brick red colored, round, film-coated tablets, debossed RX792 on one side and plain on the other side.

Simvastatin Tablets 80 mg are brick red colored, round, film-coated tablets, debossed RX793 on one side and plain on the other side.

They are supplied by State of Florida DOH Central Pharmacy as follows:

NDC | Strength | Quantity/Form | Color | Source Prod. Code
53808-0793-1 | 20 mg | 30 Tablets in a Blister Pack | Tan color | 63304-791

Storage

Store at 20 - 25° C (68 - 77° F). (See USP Controlled Room Temperature).

Manufactured for:

Ranbaxy Pharmaceuticals Inc.

Jacksonville, FL 32257 USA

This Product was Repackaged By:

State of Florida DOH Central Pharmacy
104-2 Hamilton Park Drive
Tallahassee, FL 32304
United States